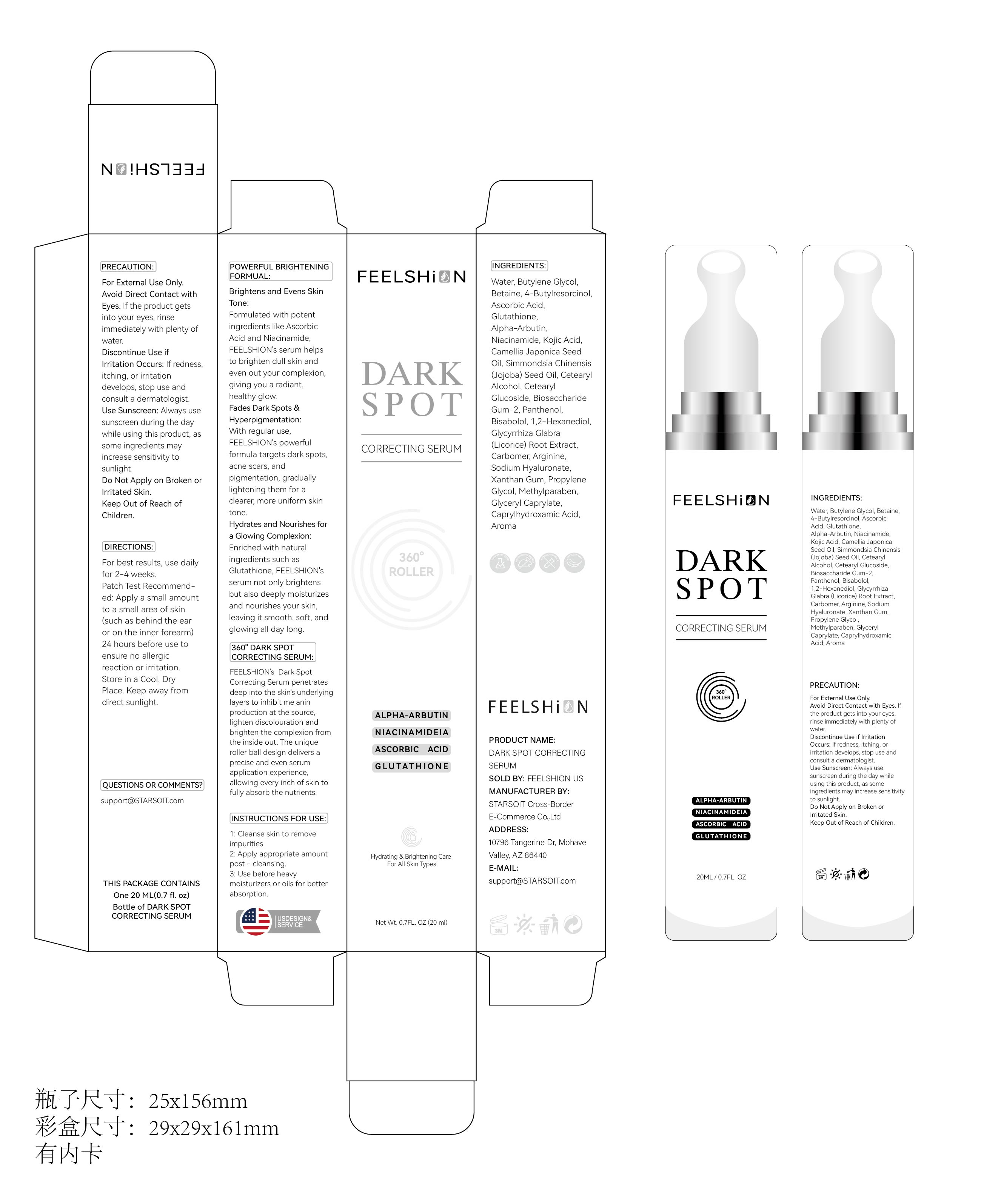 DRUG LABEL: FEELSHION Dark Spot Remover Serum
NDC: 85212-0007 | Form: LIQUID
Manufacturer: Beijing JUNGE Technology Co., Ltd.
Category: otc | Type: HUMAN OTC DRUG LABEL
Date: 20250218

ACTIVE INGREDIENTS: KOJIC ACID 1 g/100 mL; ASCORBIC ACID 2 g/100 mL; GLUTATHIONE 1 g/100 mL; NIACINAMIDE 1 g/100 mL
INACTIVE INGREDIENTS: GLYCERYL CAPRYLATE 0.1 mL/100 mL; WATER 78.5 mL/100 mL; PROPYLENE GLYCOL 0.1 mL/100 mL; CAPRYLHYDROXAMIC ACID 0.1 mL/100 mL; CAMELLIA JAPONICA SEED OIL 1 mL/100 mL; 1,2-HEXANEDIOL 0.5 mL/100 mL; 4-BUTYLRESORCINOL 2 mL/100 mL; BUTYLENE GLYCOL 5 mL/100 mL; BETAINE 2 mL/100 mL; BISABOLOL 0.5 mL/100 mL; SODIUM HYALURONATE 0.5 mL/100 mL; SIMMONDSIA CHINENSIS (JOJOBA) SEED OIL 1 mL/100 mL; CETEARYL ALCOHOL 1 mL/100 mL; CETEARYL GLUCOSIDE 1 mL/100 mL; BIOSACCHARIDE GUM-2 1 mL/100 mL; PANTHENOL 0.5 mL/100 mL; XANTHAN GUM 0.1 mL/100 mL; METHYLPARABEN 0.1 mL/100 mL

PURPOSE

Uses：
For facial whitening and dark spot repair
Indications: For facial whitening and dark spot repair

INACTIVE INGREDIENT

WATER

BUTYLENE GLYCOL

BETAINE
4-BUTYLRESORCINOL
CAMELLIA JAPONICA SEED OIL
SIMMONDSIA CHINENSIS (JOJOBA) SEED OIL
CETEARYL ALCOHOL
CETEARYL GLUCOSIDE
BIOSACCHARIDE GUM-2
PANTHENOL
BISABOLOL
1,2-HEXANEDIOL
XANTHAN GUM
PROPYLENE GLYCOL
METHYLPARABEN
GLYCERYL CAPRYLATE
CAPRYLHYDROXAMIC ACID

WARNINGS

1、Before use, perform a skin test on your arm and discontinue use if you have allergy symptoms or skin abnormalities.
2、For external use only, avoid contact with eyes when used
3、Keep out of reach of children

INDICATIONS & USAGE

Apply the Body Serum to
your body or add a drop into your body
lotion and massage gently until it’s
absorb. Use Morning and evening after
bath.

KEEP OUT OF REACH OF CHILDREN

ACTIVE INGREDIENT

ASCORBIC ACID 2%
GLUTATHIONE 1%
NIACINAMIDE 1%
KOJIC ACID 1%
SODIUM HYALURONATE 0.5%

DOSAGE & ADMINISTRATION

Use Morning and evening after bath.